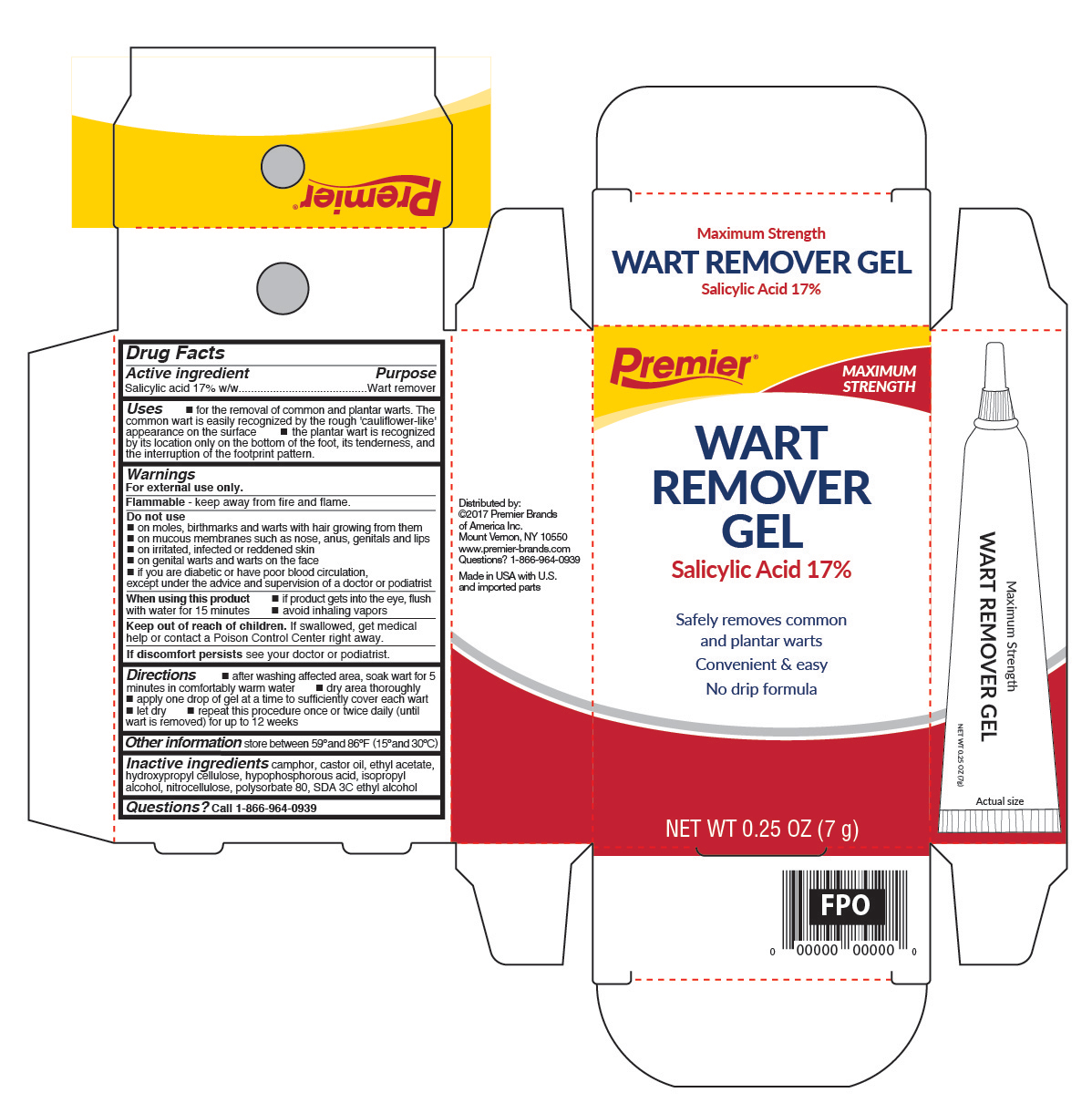 DRUG LABEL: Wart Remover Gel
NDC: 56104-237 | Form: GEL
Manufacturer: Premier Brands of America Inc.
Category: otc | Type: HUMAN OTC DRUG LABEL
Date: 20250415

ACTIVE INGREDIENTS: SALICYLIC ACID 0.17 g/1 g
INACTIVE INGREDIENTS: CAMPHOR (NATURAL); ALCOHOL; ETHYL ACETATE; HYPOPHOSPHOROUS ACID; HYDROXYPROPYL CELLULOSE (1600000 WAMW); POLYSORBATE 80; PYROXYLIN

Premier Brands Wart Remover Gel

Active ingredient

Salicylic acid 17%w/w

Purpose

Wart remover

Use

- for the removal of common and plantar warts. The common wart is easily recognized by the rough 'cauliflower-like' appearance of the surface.
- Plantar wart is recognized by its location only on the bottom of the foot, its tenderness and the interruption of the footprint pattern.

Warnings

For external use only.

Flammable

- keep away from fire and flame

Do not use

- if you are a diabetic or have poor blood circulation, except under the advice and supervision of a doctor or podiatrist

Do not use on

- moles, birthmarks and warts with hair growing from them
- mucous membranes such as nose, anus, genitals and lips
- irritated, infected or reddened skin
- genital warts and warts on the face

When using this product

- if product gets into the eyes, flush with water for 15 minutes
- avoid inhaling vapors

if discomforts persists see your doctor or podiatrist

Keep out of reach of children.

If swallowed, get medical help or contact a Poison Control Center right away.

Directions

- after washing affected area, soak wart in for 5 minutes in comfortably warm water
- dry area thoroughly
- gently squeeze a drop of gel from tube and apply to wart. Apply one drop at a time to sufficiently cover each wart
- let dry
- repeat this procedure once or twice daily (until wart is removed) for up to 12 weeks

Other information

store between 59°F to 86°F (15°C to 30°C)

Inactive ingredients

camphor, castro oil, ethyl acetate, hydroxypropyl cellulose, hypophosphorous acid, isopropyl alcohol, nitrocellulose, polysorbate 80, SDA 3C ethyl alcohol

Questions?

call 1-866-964-0939

Principal Display Panel

Premier
Maximum Strength
Wart Remover
Fast Acting Gel

- Removes common and plantar warts
- Convenient & easy
- No drip formula
- Safe & Effective

Net Wt 0.25 OZ (7 g)